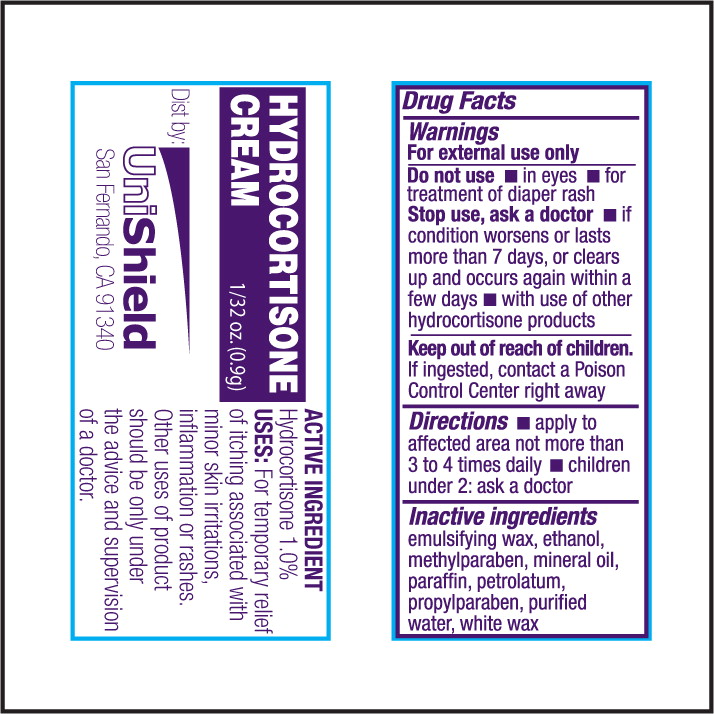 DRUG LABEL: Hydrocortisone
NDC: 49314-5801 | Form: CREAM
Manufacturer: UniShield
Category: otc | Type: HUMAN OTC DRUG LABEL
Date: 20100728

ACTIVE INGREDIENTS: Hydrocortisone 10 mg/1 mL
INACTIVE INGREDIENTS: alcohol; methylparaben; mineral oil; paraffin; petrolatum; propylparaben; water; cetostearyl alcohol; polysorbate 60; PEG-150 distearate; steareth-20

HYDROCORTISONE CREAM

Drug Facts

Warnings

For external use only

Do not use

- in eyes
- for treatment of diaper rash

Stop use, as a doctor

- if condition worsens or lasts more than 7 days, or clears up and occurs again within a few days
- with use of other hydrocortisone products

Keep out of reach of children.

If ingested, contact a Poison Control Center right away

Directions

- apply to affected area not more than 3 to 4 times daily
- children under 2: ask a doctor

Inactive ingredients

Emulsifying wax, ethanol, methylparaben, mineral oil, paraffin, petrolatum, propylparaben, purified water, white wax

ACTIVE INGREDIENT

Hydrocortisone 1.0%

USES:

For temporary relief of itching associated with minor skin irritations, inflammation or rashes. Other uses of product should be only under the advice and supervision of a doctor.

PRINCIPLE DISPLAY PANEL

HYDROCORTISONE CREAM

1/32 oz. (0.9g)

Dist by:UniShield

San Fernando, CA 91340

ACTIVE INGREDIENT

Hydrocortisone 1.0%

USES: For temporary relief

of itching associated with

minor skin irritations, inflammation or rashes.

Other uses of product

should be only under

the advice and supervision

of a doctor.